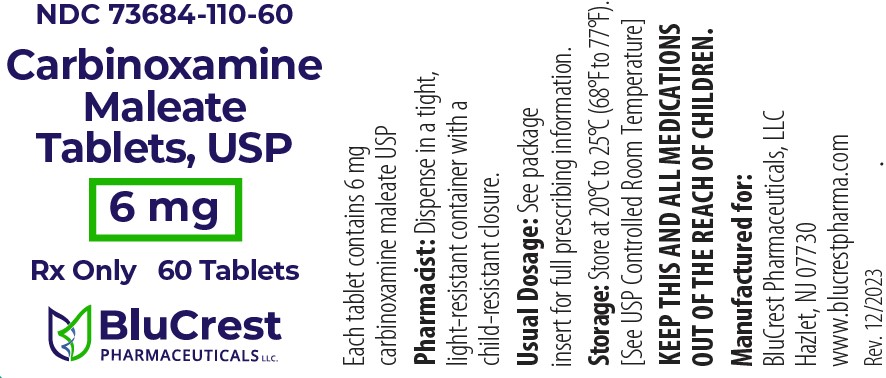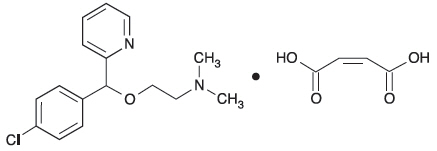 DRUG LABEL: Carbinoxamine Maleate
NDC: 73684-110 | Form: TABLET
Manufacturer: BluCrest Pharmaceuticals, LLC
Category: prescription | Type: HUMAN PRESCRIPTION DRUG LABEL
Date: 20260106

ACTIVE INGREDIENTS: CARBINOXAMINE MALEATE 6 mg/1 1
INACTIVE INGREDIENTS: ANHYDROUS LACTOSE; MICROCRYSTALLINE CELLULOSE; MAGNESIUM STEARATE; SODIUM STARCH GLYCOLATE TYPE A POTATO

Carbinoxamine Maleate
Tablets, USP 6 mg

DESCRIPTION

Carbinoxamine maleate is a histamine-H1receptor blocking agent.

Each tablet contains 6 mg carbinoxamine maleate and the following inactive ingredients: anhydrous lactose, magnesium stearate, microcrystalline cellulose, and sodium starch glycolate.

Carbinoxamine maleate is freely soluble in water. Its structure is:

2-[(4-chlorophenyl)-2-pyridinylmethoxy]-N, N-dimethylethanamine (Z)-2-butenedioate (1:1)

C16H19ClN2O∙C4H4O4 | MW=406.86

CLINICAL PHARMACOLOGY

Mechanism of Actions

Carbinoxamine maleate, an ethanolamine derivative, is an antihistamine with anticholinergic (drying) and sedative properties. Carbinoxamine appears to compete with histamine (type H1) for receptor sites on effector cells in the gastrointestinal tract, blood vessels and respiratory tract.

Pharmacokinetics and Metabolism

Carbinoxamine is well absorbed from the GI tract and appears to be extensively metabolized by the liver, and excreted in the urine as inactive metabolites within 24 hours. Virtually no intact drug is extended in the urine.

In a study comparing a controlled release suspension and a solution of carbinoxamine, healthy volunteers were administered a single dose of 8 mg carbinoxamine. A time to maximum concentration (Tmax) was between 1.5 hours to 5 hours, a peak plasma concentration (Cmax) of about 24 ng/mL was observed, and extent of exposure (AUC) was about 286 ng hr/mL. The serum half-life is reported to be 10 to 20 hours.

Drug/Food Interactions

Carbinoxamine should not be used in patients with hypersensitivity to carbinoxamine. Carbinoxamine may increase the effects of other drugs such as barbiturates, TCAs, MAO inhibitors such as Phenelzine (Nardil), Tranylcypromine (Parnate), or Selegiline (Eldepryl), alcohol, other antihistamines, and CNS depressants. Carbinoxamine can be taken with or without food.

Cardiovascular Effects

Cardiac effects, including prolongation of QT interval have not been adequately studied. Unlike other newer antihistamines, severe adverse cardiovascular effects are uncommon, and usually limited to over dosage situations.

Special Populations

Pediatric Patients

Carbinoxamine should not be used in newborn or premature infants. Neonates have an increased susceptibility to anticholinergic side effects, such as CNS excitation, which may lead to convulsions.

Pregnancy and Lactation

Safe use of carbinoxamine during pregnancy has not been established. Therefore, carbinoxamine should not be used in women who are, or may become pregnant. Carbinoxamine is in the FDA pregnancy Category C. Women who are breast-feeding should avoid use of carbinoxamine, since small amounts appear to be distributed into breast milk.

Geriatric Patients

Carbinoxamine is more likely to cause dizziness, sedation, and hypotension in elderly patients. The incidence of adverse reactions is higher in the elderly; therefore, a dosing adjustment may be necessary in this subpopulation.

INDICATIONS AND USAGE

Carbinoxamine maleate is effective for the symptomatic treatment of:

Seasonal and perennial allergic rhinitis.

Vasomotor rhinitis.

Allergic conjunctivitis due to inhalant allergens and foods.

Mild, uncomplicated allergic skin manifestations of urticaria and angioedema.

Dermatographism.

As therapy for anaphylactic reactions adjunctive to epinephrine and other standard measures after the acute manifestations have been controlled.

Amelioration of the severity of allergic reactions to blood or plasma.

CONTRAINDICATIONS

Carbinoxamine maleate is contraindicated in children younger than 2 years of age.

Carbinoxamine maleate is contraindicated in nursing mothers.

Carbinoxamine maleate is contraindicated in patients who are hypersensitive to the drug or on monoamine oxidase inhibitor therapy (see Drug Interactions).

WARNINGS

Deaths have been reported in children less than 2 years of age who were taking antihistamines, including carbinoxamine-containing drug products, therefore, carbinoxamine maleate is contraindicated in children younger than 2 years of age (see CONTRAINDICATIONS).

Antihistamines should be used with considerable caution in patients with: narrow angle glaucoma, stenosing peptic ulcer, symptomatic prostatic hypertrophy, bladder neck obstruction, pyloroduodenal obstruction.

PRECAUTIONS

General

As many other antihistamines, carbinoxamine maleate has an atropine-like action and, therefore, should be used with caution in patients with: increased intraocular pressure, hyperthyroidism, cardiovascular disease, hypertension.

Antihistamines such as carbinoxamine maleate should not be used to treat lower respiratory tract symptoms, including asthma.

Information for Patients

Carbinoxamine maleate may cause drowsiness; alcohol, sedatives, and tranquilizers may increase the drowsiness effect. Avoid alcoholic beverages while taking this product. Do not take this product if you are taking sedatives or tranquilizers, without first consulting your doctor. Use caution when driving a motor vehicle or operating machinery.

Drug Interactions

Monoamine oxidase inhibitors prolong and intensify the anticholinergic (drying) effects of antihistamines. Carbinoxamine maleate has additive effects with alcohol and other CNS depressants (hypnotics, sedatives, tranquilizers, etc.).

Carcinogenesis, Mutagenesis, Impairment of Fertility

No long-term studies in animals have been performed to determine the possible effects of carbinoxamine maleate on carcinogenesis, mutagenesis, and fertility.

Pregnancy

Teratogenic Effects

Pregnancy Category C

Animal reproductive studies have not been conducted with carbinoxamine maleate. It is also not known whether carbinoxamine maleate can cause fetal harm when administered to a pregnant woman or can affect reproductive capacity. Carbinoxamine maleate should be given to a pregnant woman only if clearly needed.

Nursing Mothers

Because of the higher risk of antihistamines for infants generally and for newborns and prematures in particular, use of carbinoxamine maleate is contraindicated in nursing mothers (see CONTRAINDICATIONS).

Pediatric Use

Carbinoxamine maleate is contraindicated in children younger than 2 years of age (see CONTRAINDICATIONS).

Neonates have an increased susceptibility to anticholinergic side effects, such as CNS excitation, which may lead to convulsions.

Carbinoxamine maleate may diminish mental alertness in children. In the young child, particularly, they may produce excitation.

Geriatric Use

Carbinoxamine maleate is more likely to cause dizziness, sedation, and hypotension in elderly patients (approximately 60 years or older). Sedating drugs may also cause confusion and over sedation in the elderly. Therefore, dose selection for an elderly patient should be cautious, usually starting at the low end of the dosing range, reflecting the greater frequency of decreased hepatic, renal, or cardiac function, and of concomitant disease or other drug therapy.

ADVERSE REACTIONS

The most frequent adverse reactions are underlined:

Body as a whole:Urticaria, drug rash, anaphylactic shock, photosensitivity, excessive perspiration, chills, dryness of mouth, nose and throat

Cardiovascular:Hypotension, headache, palpitations, tachycardia, extrasystoles

Hematologic:Hemolytic anemia, thrombocytopenia, agranulocytosis

Central nervous system: Sedation, sleepiness, dizziness, disturbed coordination, fatigue, confusion, restlessness, excitation, nervousness, tremor, irritability, insomnia, euphoria, paresthesia, blurred vision, diplopia, vertigo, tinnitus, acute labyrinthitis, hysteria, neuritis, convulsions

Gastrointestinal: Epigastric distress, anorexia, nausea, vomiting, diarrhea, constipation

Urogenital:Urinary frequency, difficult urination, urinary retention, early menses

Respiratory: Thickening of bronchial secretions, tightness of chest and wheezing, nasal stuffiness.

Call your doctor for medical advice about side effects. To report side effects, contact BluCrest Pharmaceuticals, LLC at 1-844-700-5011.

OVERDOSAGE

Manifestations

Antihistamine overdosage reactions may vary from central nervous system depression to stimulation. Stimulation is particularly likely in children. Atropine-like signs and symptoms - dry mouth; fixed, dilated pupils; flushing; and gastrointestinal symptoms may also occur.

Especially in infants and children, antihistamine overdosage may cause hallucinations, convulsions, or death.

The oral LD50of carbinoxamine maleate in guinea pigs is 411 mg/kg.

Treatment

The treatment of overdosage with carbinoxamine maleate is essentially symptomatic and supportive. Vital signs (including respiration, pulse, blood pressure, and temperature) and EKG should be monitored. Induction of vomiting is not recommended. Activated charcoal should be given and gastric lavage should be considered after ingestion of a potentially life-threatening amount of drug. In the presence of severe anticholinergic effects, physostigmine may be useful. Vasopressors may be used to treat hypotension.

DOSAGE AND ADMINISTRATION

Carbinoxamine maleate is contraindicated in children younger than 2 years of age (see CONTRAINDICATIONS).

Carbinoxamine maleate should be taken on an empty stomach with water.

DOSAGE SHOULD BE INDIVIDUALIZED ACCORDING TO THE NEEDS AND THE RESPONSE OF THE PATIENT.

Carbinoxamine maleate dosage should be based on the severity of the condition and the response of the patient. The drug is well tolerated in adults in doses as high as 24 mg daily, in divided doses, over prolonged periods. On the other hand, some patients respond to as little as 4 mg daily.

Clinical experience suggests the following dosage schedule:

Usual Adult Dosage: 1 tablet (6 mg) 3 to 4 times daily.

HOW SUPPLIED

Carbinoxamine maleate tablets, USP, 6 mg are supplied as a white, round tablet, debossed "404" on one side and "ADG" on the other side, in bottles of 60 tablets, NDC 73684-110-60.

STORAGE AND HANDLING

Store at 20° to 25°C (68° to 77°F) [see USP Controlled Room Temperature].

Dispense in a tight, light-resistant container with a child-resistant closure as defined in the official compendium.

Rx only

Manufactured for:

BluCrest Pharmaceuticals, LLC

Halet, NJ 07730

IN0110

Rev. 12/2023

PRINCIPAL DISPLAY PANEL - 6 mg Tablet Bottle Label

NDC 73684-110-60

Carbinoxamine Maleate Tablets USP, 6 mg

Rx Only
60 Tablets

BluCrest Pharmaceuticals, LLC